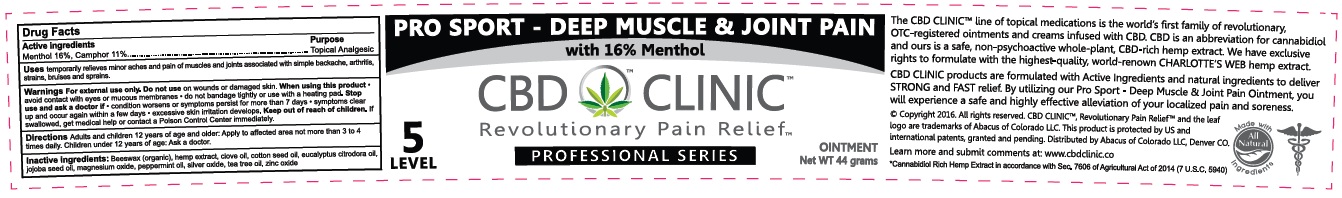 DRUG LABEL: CBD Clinic Pro Sport - Deep Muscle and Joint Pain
NDC: 24909-705 | Form: OINTMENT
Manufacturer: Aidance Skincare & Topical Solutions, LLC
Category: otc | Type: HUMAN OTC DRUG LABEL
Date: 20160714

ACTIVE INGREDIENTS: MENTHOL 16 g/100 g; CAMPHOR (SYNTHETIC) 11 g/100 g
INACTIVE INGREDIENTS: CLOVE OIL; COTTONSEED OIL; EUCALYPTUS OIL; HEMP; JOJOBA OIL; MAGNESIUM OXIDE; PEPPERMINT OIL; SILVER OXIDE; TEA TREE OIL; WHITE WAX; ZINC OXIDE

Drug Facts

Active Ingredients

Menthol 16%, Camphor 11%

Purpose

Menthol, Camphor - Topical Anesthetic

Uses

Temporarily relieves minor aches and pain of muscles and joints associated with simple backache, arthritis, strains, bruises and sprains.

Warnings

For external use only. Do not use on wounds or damaged skin. When using this product - avoid contact with eyes or mucous membranes - do not bandage tightly or use with heating pad. Stop use and ask a doctor if - condition worsens or symptoms persist for more than 7 days - symptoms clear up and occur again within a few days - excessive skin irritation develops.

Keep out of reach of children.

If swallowed, get medical help or contact a Poison Control Center immediately.

Directions

Adults and children 12 years of age and older: Apply to affected area not more than 3 to 4 times daily. Children under 12 years of age: Ask a doctor.

Inactive Ingredients

Beeswax (organic), hemp extract, clove oil, cotton seed oil, eucalyptus citrodora oil, jojoba seed oil, magnesium oxide, peppermint oil, silver oxide, tea tree oil, zinc oxide.

PRINCIPAL DISPLAY PANEL - 44g Label

PRO SPORT - DEEP MUSCLE & JOINT PAIN

with 16% Menthol

CBD CLINIC

Revolutionary Pain Relief

Level 5 PROFESSIONAL SERIES Ointment Net WT 44 grams